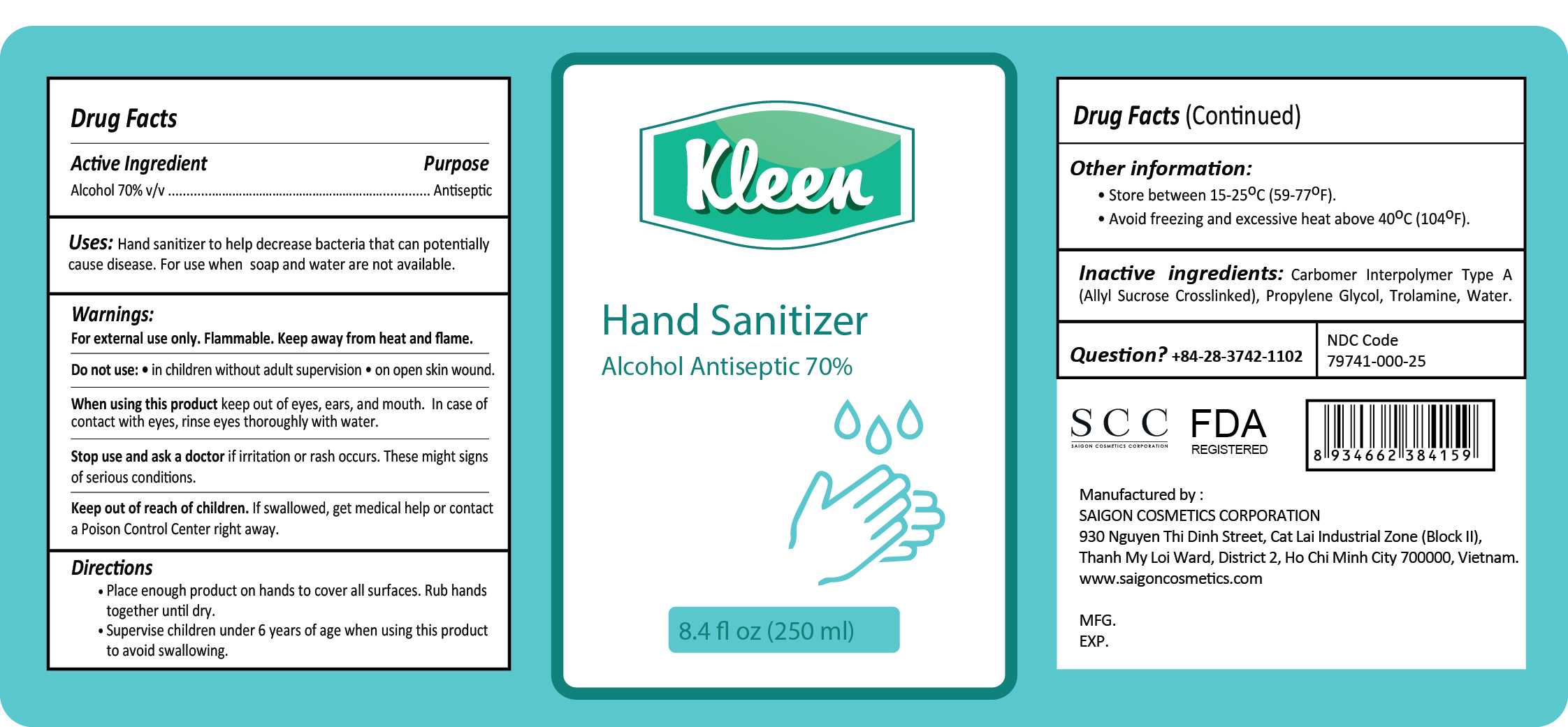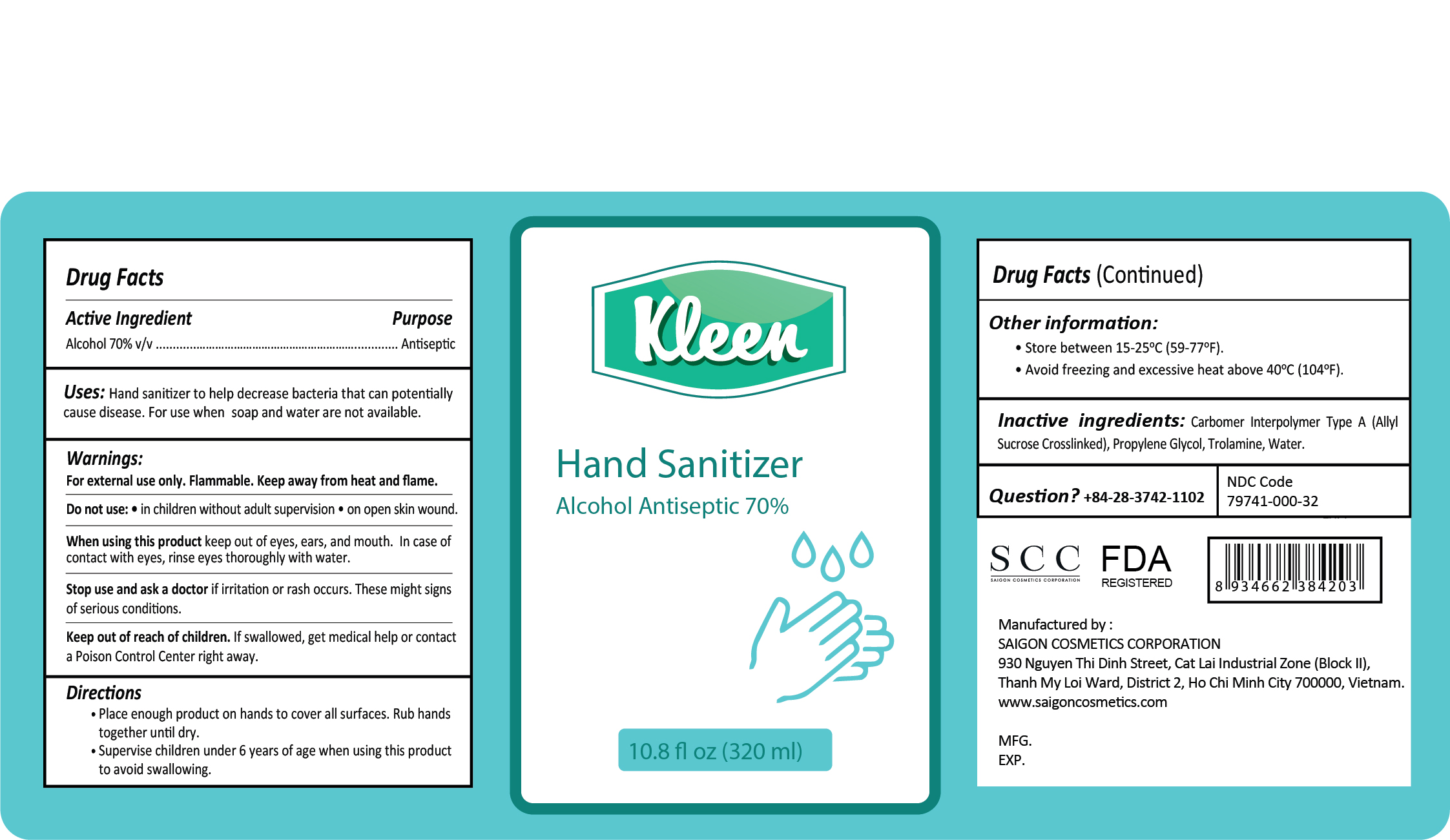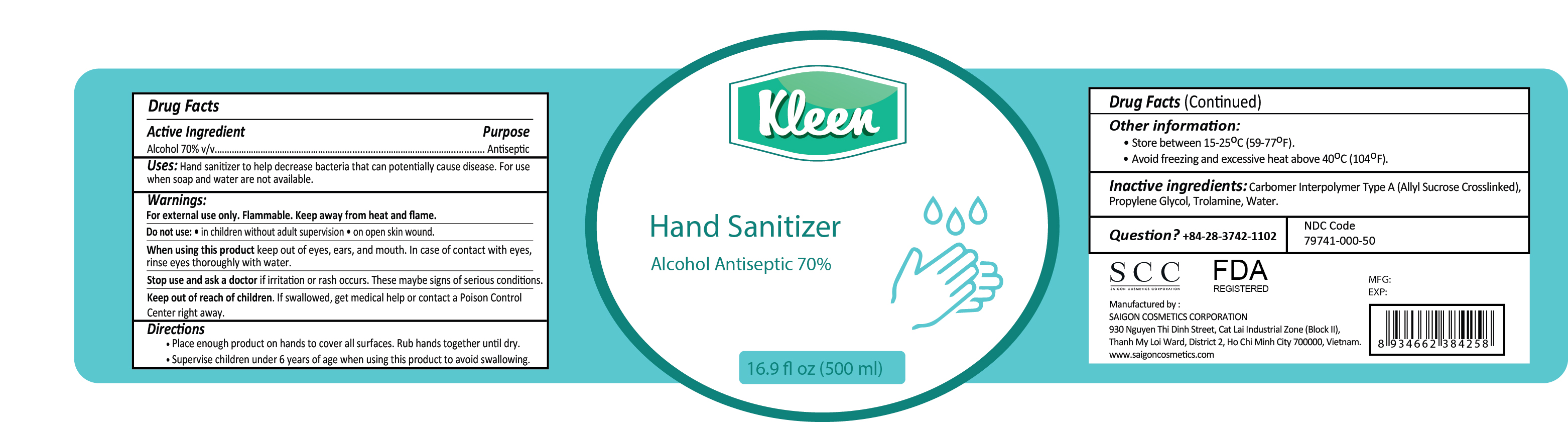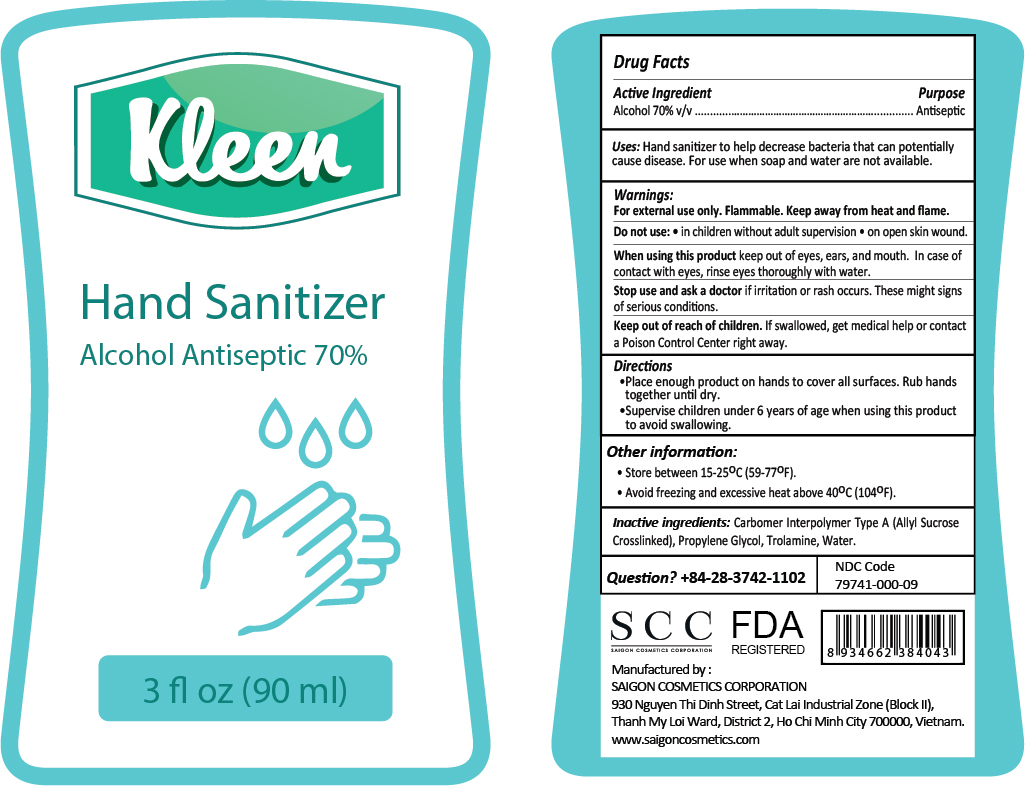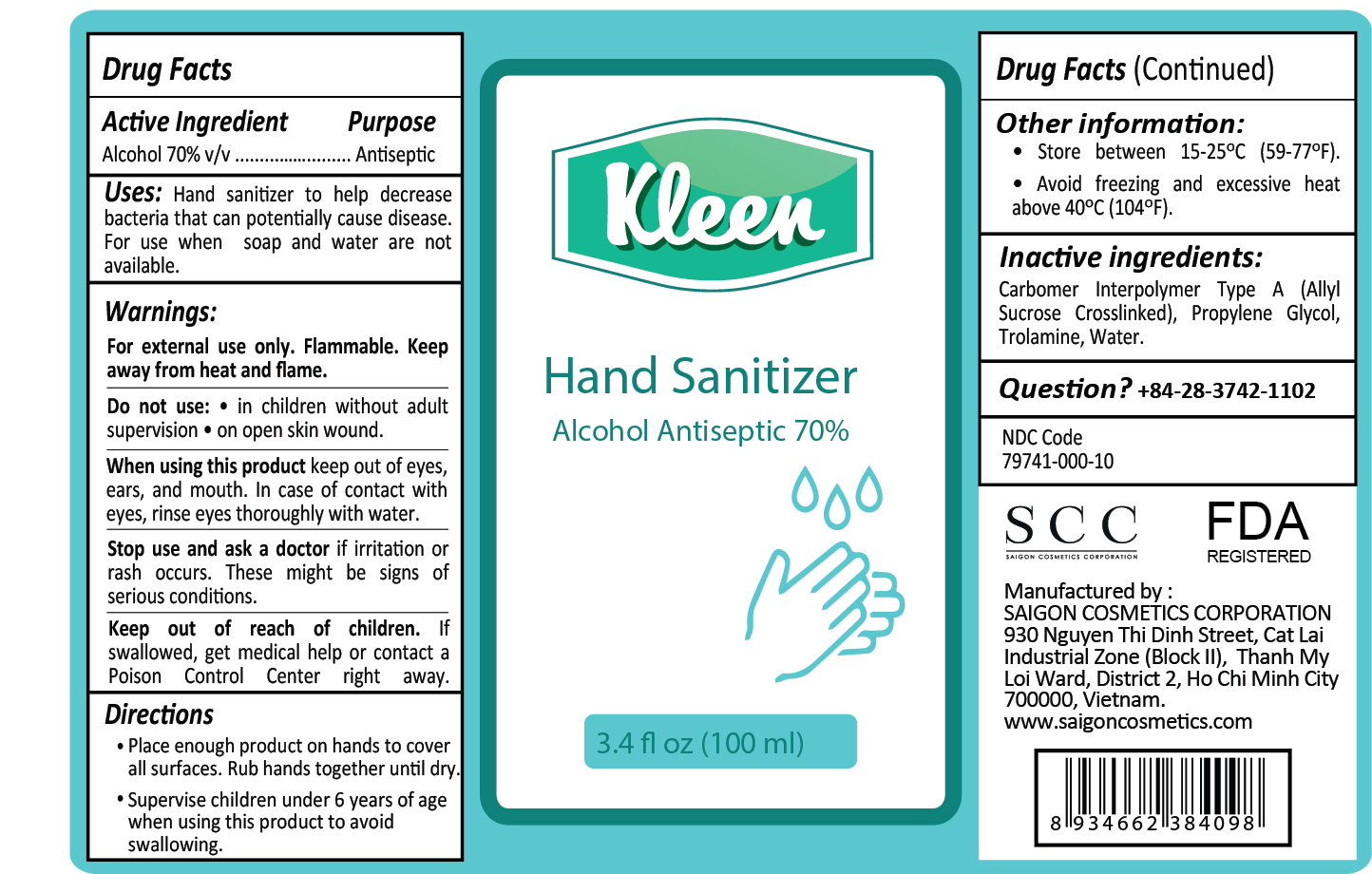 DRUG LABEL: KLEEN HAND SANITIZER
NDC: 79741-000 | Form: GEL
Manufacturer: 79741
Category: otc | Type: HUMAN OTC DRUG LABEL
Date: 20200825

ACTIVE INGREDIENTS: ALCOHOL 70 mL/100 mL
INACTIVE INGREDIENTS: CARBOMER INTERPOLYMER TYPE A (ALLYL SUCROSE CROSSLINKED); TROLAMINE; WATER; PROPYLENE GLYCOL

ACTIVE INGREDIENT

Alcohol 70% v/v Purpose: Antiseptic

PURPOSE

Antiseptic, Hand Sanitizer

INDICATIONS AND USAGE

Hand sanitizer to help decrease bacteria that can potentially cause disease. For use when soap and water are not available.

WARNINGS

For external use only. Flammable. Keep away from heat and flame.

Do not use

- In children without aldult supervision
- On open skin wound

When using this product keep out of eyes, ears, and mouth. In case of contact with eyes, rinse eyes thoroughly with water.

Stop use and ask a doctor if irritation or rash occurs. These may be signs of serious conditions.

Keep out of reach of children. If swallowed, get medical help or contact a Poison Control Center right away.

Directions:

· Place enough product on hands to cover all surfaces. Rub hands together until dry.

· Supervise children under 6 years of age when using this product to avoid swallowing.

Other information:

- Store between 15-25oC (59-77oF)
- Avoid freezing and excessive heat above 40oC (104oF)

INACTIVE INGREDIENT

Carbomer Interpolymer Type A (Allyl Sucrose Crosslinked), Propylene Glycol, Trolamine, Water

QUESTIONS

+84-28-3742-1102

PACKAGE LABEL

Kleen Hand Sanitizer 90mL

Kleen Hand Sanitizer 100mL

Kleen Hand Sanitizer 250mL

Kleen Hand Sanitizer 320mL

Kleen Hand Sanitizer 500mL